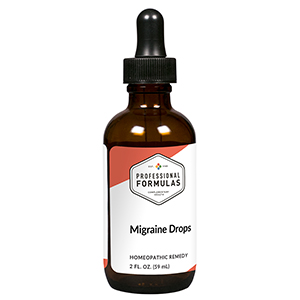 DRUG LABEL: Migraine Drops
NDC: 63083-2140 | Form: LIQUID
Manufacturer: Professional Complementary Health Formulas
Category: homeopathic | Type: HUMAN OTC DRUG LABEL
Date: 20190815

ACTIVE INGREDIENTS: SPIGELIA ANTHELMIA WHOLE 2 [hp_X]/59 mL; CYCLAMEN PURPURASCENS TUBER 3 [hp_X]/59 mL; CLAVICEPS PURPUREA SCLEROTIUM 3 [hp_X]/59 mL; TANACETUM VULGARE TOP 3 [hp_X]/59 mL; AMARYLLIS BELLADONNA WHOLE 4 [hp_X]/59 mL; BRYONIA ALBA ROOT 4 [hp_X]/59 mL; GELSEMIUM SEMPERVIRENS ROOT 6 [hp_X]/59 mL; NITROGLYCERIN 6 [hp_X]/59 mL; IRIS VERSICOLOR ROOT 6 [hp_X]/59 mL; TANACETUM PARTHENIUM WHOLE 6 [hp_X]/59 mL
INACTIVE INGREDIENTS: ALCOHOL; WATER

C140

ACTIVE INGREDIENTS

Spigelia anthelmia 2X
Cyclamen europaeum 3X
Secale cornutum 3X
Tanacetum vulgare 3X
Belladonna 4X
Bryonia 4X
Gelsemium sempervirens 6X
Glonoinum 6X
Iris versicolor 6X
Tanacetum parthenium 6X

QUESTIONS

Professional Formulas

PO Box 2034 Lake Oswego, OR 97035

INDICATIONS

For the temporary relief of headache, sensitivity to light or sound, or nausea.*

PURPOSE

*Claims based on traditional homeopathic practice, not accepted medical evidence. Not FDA evaluated.

WARNINGS

Consult a doctor if condition worsens or if symptoms persist. Keep out of the reach of children. In case of overdose, get medical help or contact a poison control center right away. If pregnant or breastfeeding, ask a healthcare professional before use.

Keep out of the reach of children.

PREGNANCY OR BREAST FEEDING

If pregnant or breastfeeding, ask a healthcare professional before use.

DIRECTIONS

Place drops under tongue 30 minutes before/after meals. Adults and children 12 years and over: Take 10 drops up to 3 times per day for up to 6 weeks. For immediate onset of symptoms, take 10 to 15 drops every 15 minutes up to 3 hours. For less severe symptoms, take 10-15 drops hourly up to 8 hours. Consult a physician for use in children under 12 years of age.

OTHER INFORMATION

Tamper resistant. If seal is broken, do not use. After opening, close container tightly and store at room temperature away from heat.

INACTIVE INGREDIENTS

20% ethanol, purified water.

LABEL

Est 1985

Professional Formulas

Complementary Health

Migraine Drops

Homeopathic Remedy

2 FL. OZ. (59 mL)